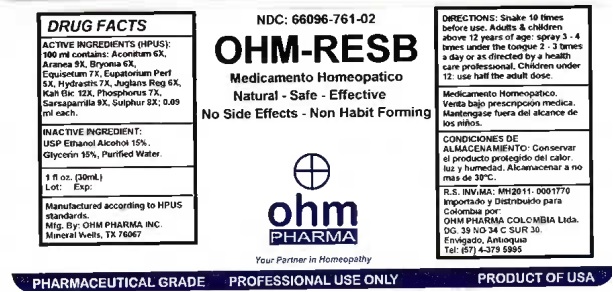 DRUG LABEL: OHM-RESB
NDC: 66096-761 | Form: SPRAY
Manufacturer: OHM PHARMA INC.
Category: homeopathic | Type: HUMAN PRESCRIPTION DRUG LABEL
Date: 20260128

ACTIVE INGREDIENTS: ACONITUM NAPELLUS 6 [hp_X]/30 mL; ARANEUS DIADEMATUS 9 [hp_X]/30 mL; BRYONIA ALBA ROOT 6 [hp_X]/30 mL; EQUISETUM HYEMALE 7 [hp_X]/30 mL; EUPATORIUM PERFOLIATUM FLOWERING TOP 5 [hp_X]/30 mL; GOLDENSEAL 7 [hp_X]/30 mL; JUGLANS REGIA LEAF 6 [hp_X]/30 mL; POTASSIUM DICHROMATE 12 [hp_X]/30 mL; PHOSPHORUS 7 [hp_X]/30 mL; SARSAPARILLA 9 [hp_X]/30 mL
INACTIVE INGREDIENTS: WATER; GLYCERIN; ALCOHOL

OHM-RESB

ACTIVE INGREDIENT

ACTIVE INGREDIENTS: (HPUS): 100 ml contains: Aconitum 6X, Aranea 9X, Bryonia 6X, Equisetum 7X, Eupatorium Perf 5X, Hydrastis 7, Juglans Reg 6X, Kali Bic 12X, Phosphorus 7X, Sarsaparilla 9X, Sulphur 8X; 0.09 ml each.

INDICATIONS AND USAGE

USES: Temporarily relieves lower respiratory track mucosa irritation or secretion due to diverse etiology.**

WARNINGS

Medicamento Homeopatico.

Venta bajo prescripcion medica.

Mantengase fuera del alcance de los niños.

KEEP OUT OF REACH OF CHILDREN

Mantengase fuera del alcance de los niños.

DOSAGE AND ADMINISTRATION

DIRECTIONS: Shake 10 times before use. Adults & children above 12 years of age: spray 3 - 4 times under the tongue 2 - 3 times a day or as directed by a health care professional. Children under 12: use half the adult dose.

OTHER SAFETY INFORMATION

CONDICIONES DE ALMACENAMIENTO: Conservar el producto protegido del calor, luz y humedad. Alcamadenar a no mas de 30°C.

INACTIVE INGREDIENT:

USP Ethanol Alcohol 15%,

Glycerin 15%, Purified Water.

QUESTIONS

Importado y distribuido para Colombia por

OHM PHARMA COLOMBIA SAS
Vereda El Abra
Sector Saunas Medicas
Finca el Rinconcito
Cota, Cundinamarca, Colombia
Tel: (+57) 320-230-7789

R.S. INVIMA: MH2011-0001770

Manufactured according to HPUS

standards.

Mfg. By: OHM PHARMA INC.

Mineral Wells, TX 76067

PACKAGE LABEL

NDC: 66096-761-02

OHM-RESB

Medicamento Homeopatico

Natural - Safe - Effective

No Side Effects - Non Habit Forming

PURPOSE

USES: Temporarily relieves lower respiratory track mucosa irritation or secretion due to diverse etiology.**